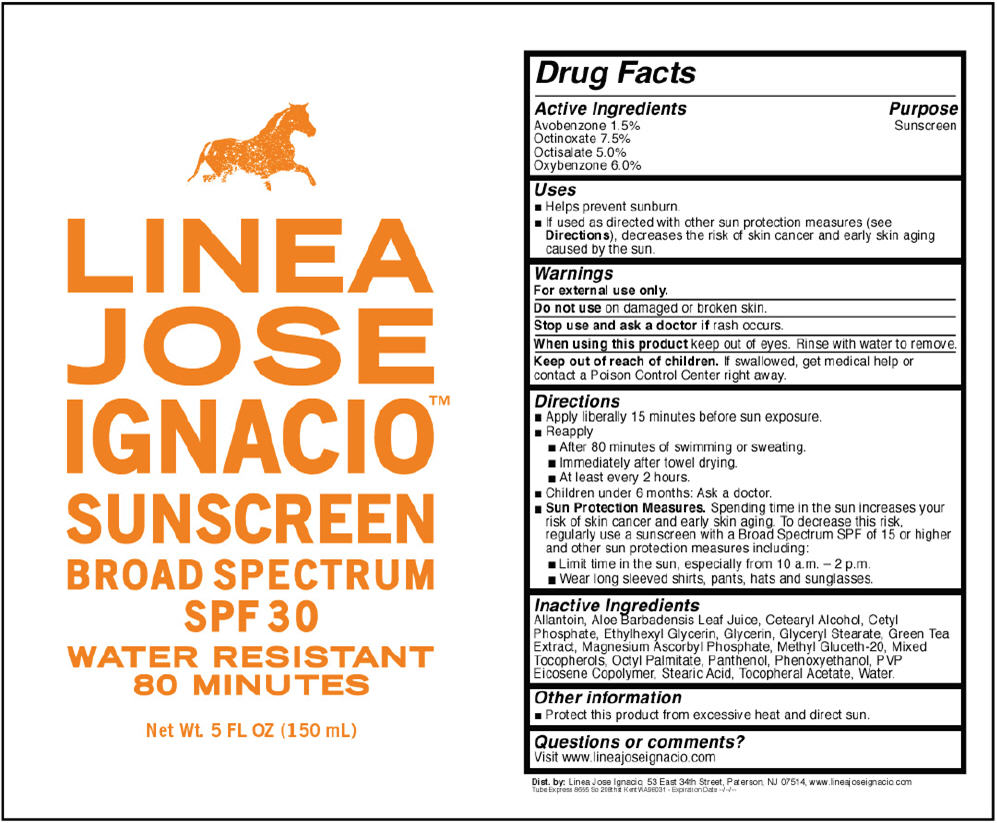 DRUG LABEL: Linea Jose Ignacio Sunscreen Broad Spectrum SPF30
NDC: 69096-0100 | Form: LOTION
Manufacturer: Linea Jose Ignacio
Category: otc | Type: HUMAN OTC DRUG LABEL
Date: 20140724

ACTIVE INGREDIENTS: Avobenzone 15 mg/1 mL; Octinoxate 75 mg/1 mL; Octisalate 50 mg/1 mL; Oxybenzone 60 mg/1 mL
INACTIVE INGREDIENTS: ALLANTOIN; ALOE VERA LEAF; CETOSTEARYL ALCOHOL; CETYL PHOSPHATE; ETHYLHEXYLGLYCERIN; GLYCERIN; GLYCERYL MONOSTEARATE; GREEN TEA LEAF; MAGNESIUM ASCORBYL PHOSPHATE; METHYL GLUCETH-20; TOCOPHEROL; ETHYLHEXYL PALMITATE; PANTHENOL; PHENOXYETHANOL; VINYLPYRROLIDONE/EICOSENE COPOLYMER; STEARIC ACID; .ALPHA.-TOCOPHEROL ACETATE; WATER

Linea Jose Ignacio™ Sunscreen Broad Spectrum SPF30

Drug Facts

Active Ingredients

Avobenzone 1.5%
Octinoxate 7.5%
Octisalate 5.0%
Oxybenzone 6.0%

Purpose

Sunscreen

Uses

- helps prevent sunburn
- if used as directed with other sun protection measures (see Directions), decreases the risk of skin cancer and early skin aging caused by the sun

Warnings

For external use only

Do not use on damaged or broken skin

Stop use and ask a doctor if rash occurs

When using this product keep out of eyes. Rinse with water to remove.

Keep out of reach of children. If swallowed, get medical help or contact a Poison Control Center right away.

Directions

- apply liberally 15 minutes before sun exposure
- reapply:
  - after 80 minutes of swimming or sweating
  - immediately after towel drying
  - at least every 2 hours
- children under 6 months: Ask a doctor
- Sun Protection Measures. Spending time in the sun increases your risk of skin cancer and early skin aging. To decrease this risk, regularly use a sunscreen with a Broad Spectrum SPF of 15 or higher and other sun protection measures including:
  - limit time in the sun, especially from 10 a.m. – 2 p.m.
  - wear long sleeved shirts, pants, hats and sunglasses

Inactive Ingredients

Allantoin, Aloe Barbadensis Leaf Juice, Cetearyl Alcohol, Cetyl Phosphate, Ethylhexyl Glycerin, Glycerin, Glyceryl Stearate, Green Tea Extract, Magnesium Ascorbyl Phosphate, Methyl Gluceth-20, Mixed Tocopherols, Octyl Palmitate, Panthenol, Phenoxyethanol, PVP Eicosene Copolymer, Stearic Acid, Tocopheral Acetate, Water

Other information

- protect this product from excessive heat and direct sun

Questions?

Visit www.lineajoseignacio.com

Dist. by:
Linea Jose Ignacio
53 East 34th Street
Paterson, NJ 07514
www.lineajoseignacio.com

PRINCIPAL DISPLAY PANEL - 150 mL Tube Label

LINEA
JOSE
IGNACIO™

SUNSCREEN

BROAD SPECTRUM
SPF 30

WATER RESISTANT
80 MINUTES

Net Wt. 5 FL OZ (150 mL)